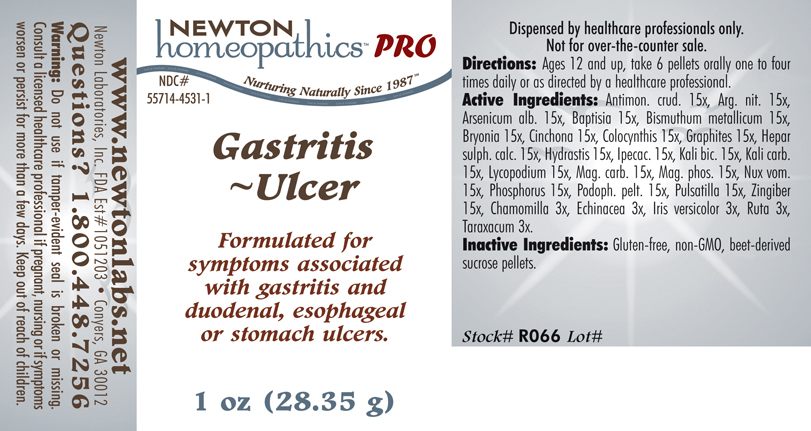 DRUG LABEL: Gastritis - Ulcer 
NDC: 55714-4531 | Form: PELLET
Manufacturer: Newton Laboratories, Inc.
Category: homeopathic | Type: HUMAN PRESCRIPTION DRUG LABEL
Date: 20110601

ACTIVE INGREDIENTS: Antimony Trisulfide 15 [hp_X]/1 g; Silver Nitrate 15 [hp_X]/1 g; Arsenic Trioxide 15 [hp_X]/1 g; Baptisia Tinctoria 15 [hp_X]/1 g; Bismuth 15 [hp_X]/1 g; Bryonia Alba Root 15 [hp_X]/1 g; Cinchona Officinalis Bark 15 [hp_X]/1 g; Citrullus Colocynthis Fruit Pulp 15 [hp_X]/1 g; Graphite 15 [hp_X]/1 g; Calcium Sulfide 15 [hp_X]/1 g; Goldenseal 15 [hp_X]/1 g; Ipecac 15 [hp_X]/1 g; Potassium Dichromate 15 [hp_X]/1 g; Potassium Carbonate 15 [hp_X]/1 g; Lycopodium Clavatum Spore 15 [hp_X]/1 g; Magnesium Carbonate 15 [hp_X]/1 g; Magnesium Phosphate, Dibasic Trihydrate 15 [hp_X]/1 g; Strychnos Nux-vomica Seed 15 [hp_X]/1 g; Phosphorus 15 [hp_X]/1 g; Podophyllum 15 [hp_X]/1 g; Pulsatilla Vulgaris 15 [hp_X]/1 g; Ginger 15 [hp_X]/1 g; Matricaria Recutita 3 [hp_X]/1 g; Echinacea, Unspecified 3 [hp_X]/1 g; Iris Versicolor Root 3 [hp_X]/1 g; Ruta Graveolens Flowering Top 3 [hp_X]/1 g; Taraxacum Officinale 3 [hp_X]/1 g
INACTIVE INGREDIENTS: Sucrose

Gastritis - Ulcer

INDICATIONS & USAGE SECTION

Gastritis - Ulcer Formulated for symptoms associated with gastritis and duodenal, esophageal or stomach ulcers.

DOSAGE & ADMINISTRATION SECTION

Directions: ORAL USE ONLY - SHAKE WELL. Ages 12 and up, take 6 pellets orally one to four times daily or as directed by a healthcare professional.

ACTIVE INGREDIENT SECTION

Antimon. crud. 15x, Arg. nit. 15x, Arsenicum alb. 15x, Baptisia 15x, Bismuthum metallicum 15x, Bryonia 15x, Cinchona 15x, Colocynthis 15x, Graphites 15x, Hepar sulph. calc. 15x, Hydrastis 15x, Ipecac. 15x, Kali bic. 15x, Kali carb.15x, Lycopodium 15x, Mag. carb. 15x, Mag. phos. 15x, Nux vom.15x, Phosphorus 15x, Podoph. pelt. 15x, Pulsatilla 15x, Zingiber 15x, Chamomilla 3x, Echinacea 3x, Iris versicolor 3x, Ruta 3x, Taraxacum 3x.

PURPOSE SECTION

Formulated for symptoms associated with gastritis and duodenal, esophageal or stomach ulcers.

INACTIVE INGREDIENT SECTION

Inactive Ingredients: Gluten-free, non-GMO, beet-derived sucrose pellets.

QUESTIONS? SECTION

www.newtonlabs.net Newton Laboratories, Inc. FDA Est # 1051203 - Conyers, GA 30012
Questions? 1.800.448.7256

WARNINGS SECTION

Warning: Do not use if tamper - evident seal is broken or missing. Consult a licensed healthcare professional if pregnant, nursing or if symptoms worsen or persist for more than a few days. Keep out of reach of children.

PREGNANCY OR BREAST FEEDING SECTION

Consult a licensed healthcare professional if pregnant, nursing or if symptoms worsen or persist for more than a few days.

KEEP OUT OF REACH OF CHILDREN SECTION

Keep out of reach of children.